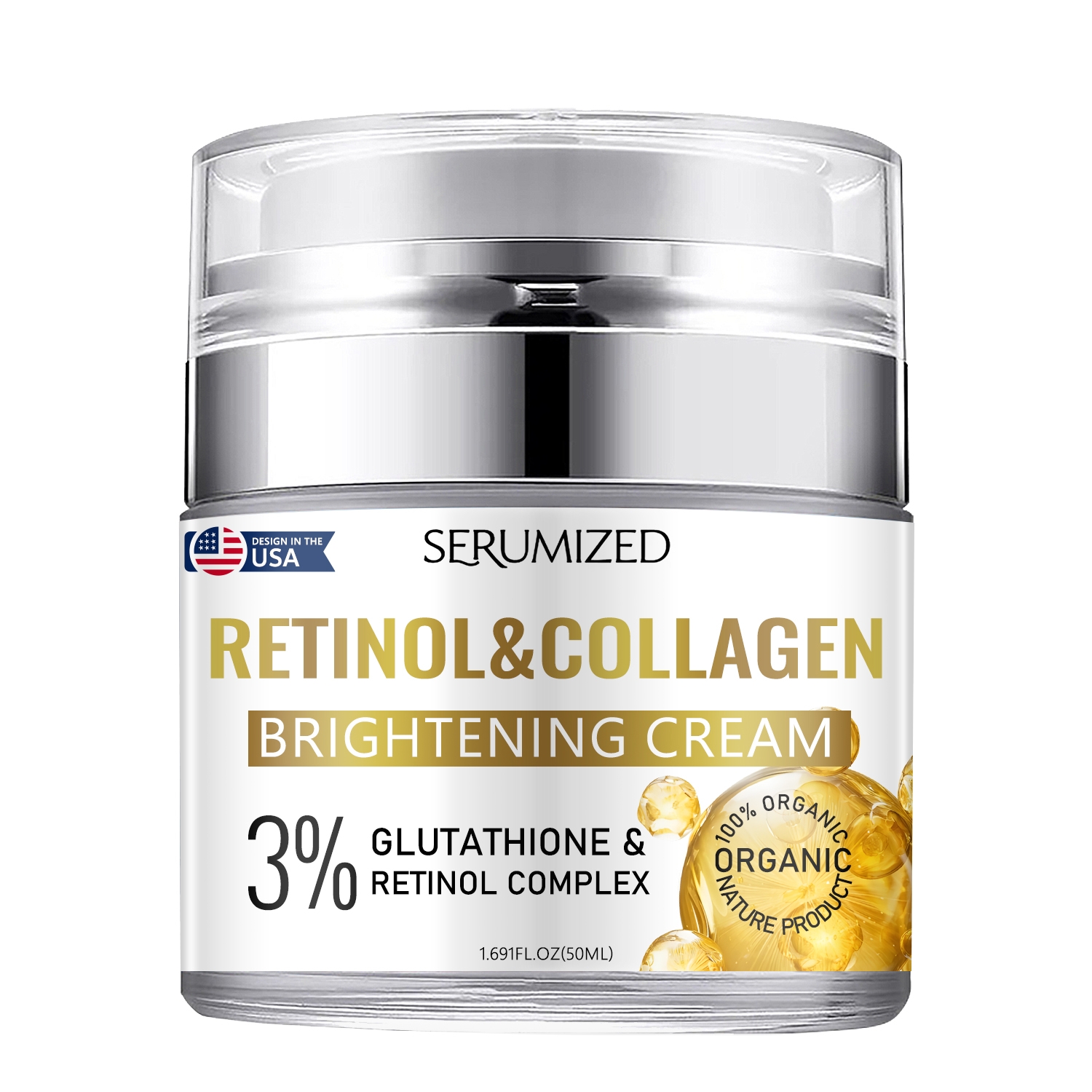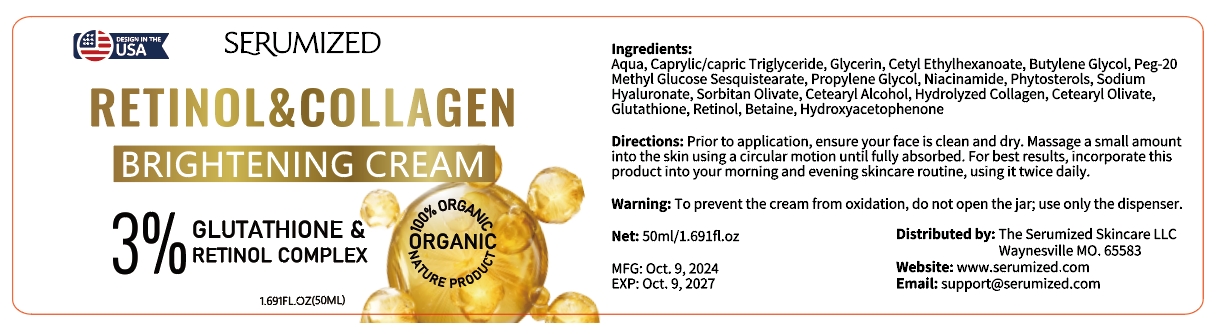 DRUG LABEL: retinol collagen brightening cream
NDC: 84025-291 | Form: CREAM
Manufacturer: Guangzhou Yanxi Biotechnology Co., Ltd
Category: otc | Type: HUMAN OTC DRUG LABEL
Date: 20241220

ACTIVE INGREDIENTS: NIACINAMIDE 4 mg/50 mL; GLYCERIN 6 mg/50 mL
INACTIVE INGREDIENTS: WATER

DOSAGE AND ADMINISTRATION

Massage a small amountinto the skin using a circular motion until fully absorbed.

WARNINGS

Keep out of children

INACTIVE INGREDIENT

Aqua

INDICATIONS AND USAGE

For daily skin care

Keep out of children

PURPOSE

Brightening skin